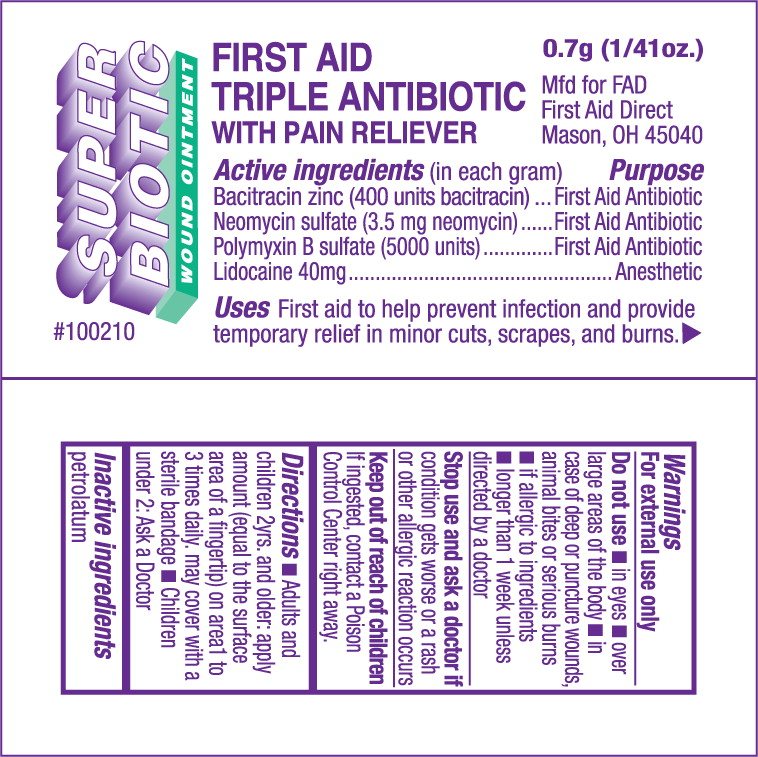 DRUG LABEL: First Aid Triple Antibiotic with Pain Reliever
NDC: 68421-6500 | Form: OINTMENT
Manufacturer: Cintas First Aid & Safety
Category: otc | Type: HUMAN OTC DRUG LABEL
Date: 20100915

ACTIVE INGREDIENTS: bacitracin zinc 400 [iU]/1 g; neomycin sulfate 3.5 mg/1 g; polymyxin b sulfate 5000 [iU]/1 g; lidocaine 40 mg/1 g
INACTIVE INGREDIENTS: petrolatum

SUPER BIOTIC WOUND OINTMENT

FIRST AID
TRIPLE ANTIBIOTIC
With PAIN RELIEVER

Active ingredients (in each gram)

Bacitracin zinc (400 units bacitracin

Neomycin sulfate (3.5 mg neomycin)

Polymyxin B sulfate (5000 units)

Lidocaine 40mg

Purpose

First Aid Antibiotic

First Aid Antibiotic

First Aid Antibiotic

Anesthetic

INDICATIONS AND USAGE

Uses First aid to help prevent infection and provide temporary relief in minor cuts, scrapes and burns.

Warnings

For external use only

Do not use

- in eyes
- over large areas of the body
- in case of deep or puncture wounds, animal bites or serious burns
- if allergic to ingredients
- longer than 1 week unless directed by a doctor

Stop use and ask a doctor if condition gets worse or a rash or other allergic reactions occurs

Keep out of reach of children If ingested, contact a Poison Control Center right away.

Directions

- Adults and children 2yrs. And older: apply amount (equal to the surface area of a fingertip) on area 1 to 3 times daily, may cover with a sterile bandage
- Children under 2: Ask a Doctor

Inactive ingredients

petrolatum

PRINCIPLE DISPLAY PANEL

SUPER
BIOTIC
WOUND OINTMENT

#100210

FIRST AID
TRIPLE ANTIBIOTIC
WITH PAIN RELIEVER

0.7g (1/41 oz.)

Mfd for FAD
First Aid Direct
Mason, OH 45040

Active ingredients (in each gram)
Bacitracin zinc (400 units Bacitracin)
Neomycin sulfate (3.5 mg neomycin)
Polymyxin B sulfate (5000 units)
Lidocaine 40 mg

Purpose
First Aid Antibiotic
First Aid Antibiotic
First Aid Antibiotic
Anesthetic

Uses First aid to help prevent infection and provide temporary relief in minor cuts, scrapes, and burns